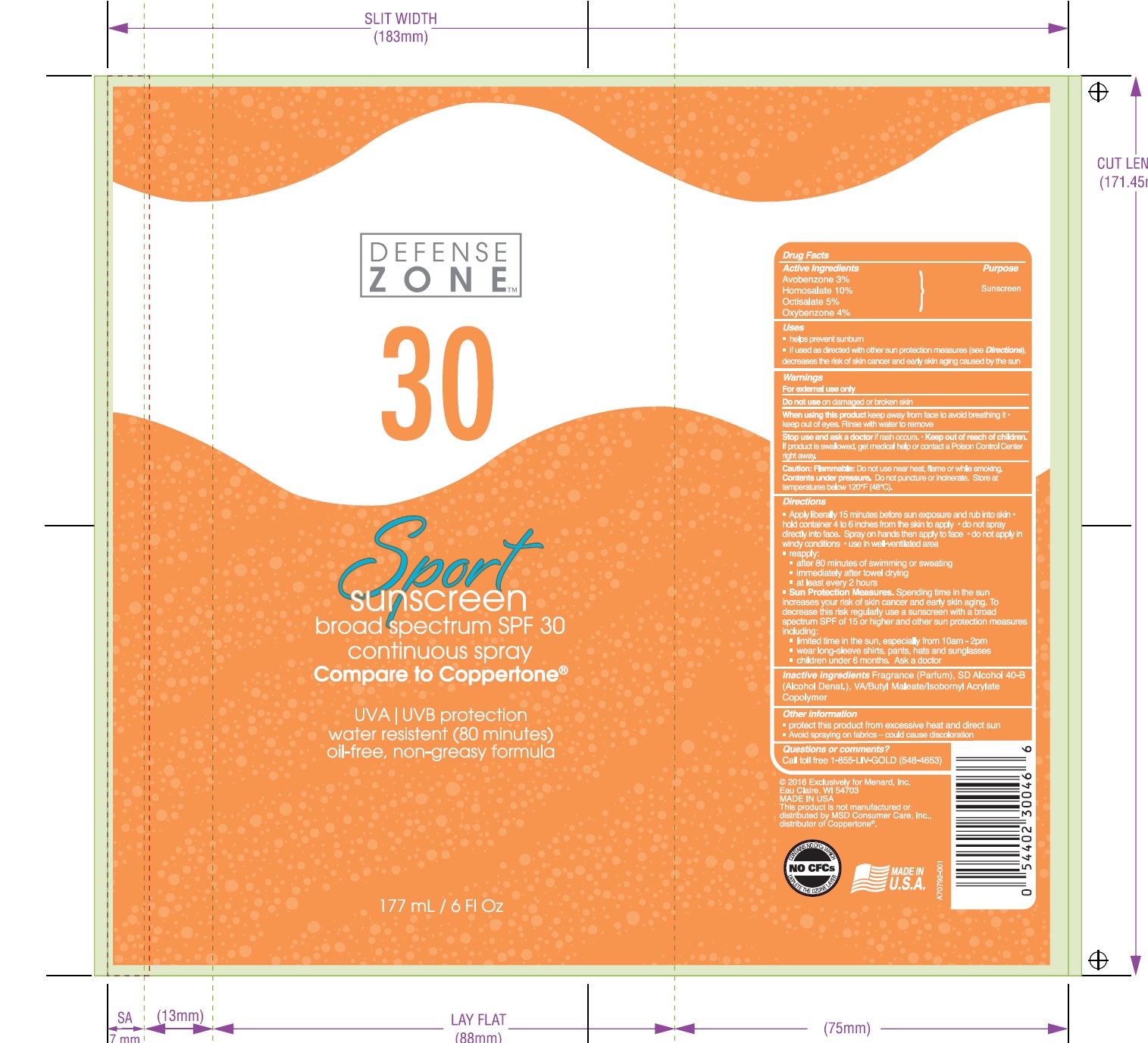 DRUG LABEL: Defense Zone
NDC: 13630-0108 | Form: SPRAY
Manufacturer: Prime Packaging Inc.
Category: otc | Type: HUMAN OTC DRUG LABEL
Date: 20200117

ACTIVE INGREDIENTS: AVOBENZONE 24.1 mg/1 mL; HOMOSALATE 80.2 mg/1 mL; OCTISALATE 40.1 mg/1 mL; OXYBENZONE 32.1 mg/1 mL
INACTIVE INGREDIENTS: BUTYL ACRYLATE/C16-C20 ALKYL METHACRYLATE/METHACRYLIC ACID/METHYL METHACRYLATE COPOLYMER; ALCOHOL

Defense Zone Sport C/S Broad Spectrum SPF 30

Active Ingredients

Avobenzone 3%

Homosalate 10%

Octisalate 5%

Oxybenzone 4%

Purpose

Sunscreen

Uses

- helps prevent sunburn
- if used as directed with other sun protection measures (see Directions), decreases the risk of skin cancer and early skin aging caused by the sun.

Warnings

For external use only

Do not use on damaged or broken skin

When using this product keep away from face to avoid breathing it

- keep out of eyes. Rinse with water to remove

Stop use and ask a doctor if rash occurs

Keep out of reach of children. If product is swallowed, get medical help or contact a Poison Control Center right away.

OTHER SAFETY INFORMATION

Caution: Flammable: Do not use near heat, flame or while smoking. Contents under pressure. Do not puncture or incinerate. Store at temperatures below 120ºF (48ºC).

Directions

- Apply liberally 15 minutes before sun exposure and rub into skin
- hold container 4 to 6 inches from the skin to apply
- do not spray directly into face. Spray on hands then apply to face
- do not apply in windy conditions
- use in well-ventilated area
- reapply:
- after 80 minutes of swimming or sweating
- immediately after towel drying
- at least every 2 hours
- Sun Protection Measures. Spending time in the sun increases your risk of skin cancer and early skin aging. To decrease this risk, regularly use a sunscreen with a broad spectrum SPF of 15 or higher and other sun protection measures including:
- limit time in the sun, especially from 10 a. m. - 2 p. m.
- wear long-sleeve shirts, pants, hats, and sunglasses
- children under 6 months: Ask a doctor

Inactive Ingredients

Fragrance (Parfum), SD Alcohol 40-B (Alcohol Denat.), VA/Butyl Maleate/Isobornyl Acrylate Copolymer

Other Information

- protect this product from excessive heat and direct sun
- Avoid spraying on fabrics - could cause discoloration

Question or comments?

Call toll free 1-855-LIV-GOLD (548-4653)